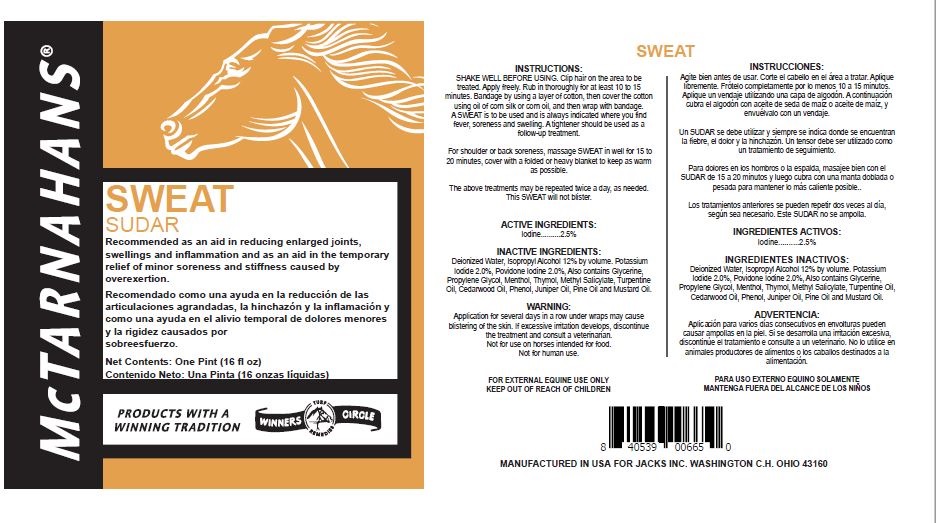 DRUG LABEL: Sweat
NDC: 61156-107 | Form: LINIMENT
Manufacturer: JACKS MFG INC
Category: animal | Type: OTC ANIMAL DRUG LABEL
Date: 20211208

ACTIVE INGREDIENTS: IODINE 0.02 g/1 mL
INACTIVE INGREDIENTS: POTASSIUM IODIDE 0.01 g/1 mL; WATER 0.09 mL/1 mL; ISOPROPYL ALCOHOL 0.11 mL/1 mL; MENTHOL 0.01 g/1 mL; THYMOL 0.000147 mL/1 mL; GLYCERIN 0.54 mL/1 mL; PROPYLENE GLYCOL 0.19 mL/1 mL; METHYL SALICYLATE 0.000147 mL/1 mL; TURPENTINE OIL 0.000147 mL/1 mL; JUNIPER BERRY OIL 0.000147 mL/1 mL; CEDAR LEAF OIL 0.000147 mL/1 mL; PINE NUT OIL 0.01 mL/1 mL; PHENOL 0.01 mL/1 mL; MUSTARD OIL 0.000147 mL/1 mL; POVIDONE-IODINE 0.01 g/1 mL

Sweat

INSTRUCTIONS:

SHAKE WELL BEFORE USING.

Clip hair on the area to be treated.

Apply freely.

Rub in thoroughly for at least 10 to 15 minutes.

Bandage by using a layer of cotton, then cover the cotton using oil of corn silk or corn oil, and then wrap with bandage.

A SWEAT is to be used and is always indicated where you find fever, soreness and swelling.

A tightener should be used as a follow-up treatment.

For shoulder or back soreness, massage SWEAT in well for 15 to 20 minutes, cover with a folded or heavy blanket to keep as warm as possible.

The above treatments may be repeated twice a day, as needed.This SWEAT will not blister.

Warnings

Application for several days in a row under wraps may cause blistering of the skin.

If excessive irritation develops, discontinue the treatment and consult a veterinarian.

Not for use on horses intended for food.Not for human use.